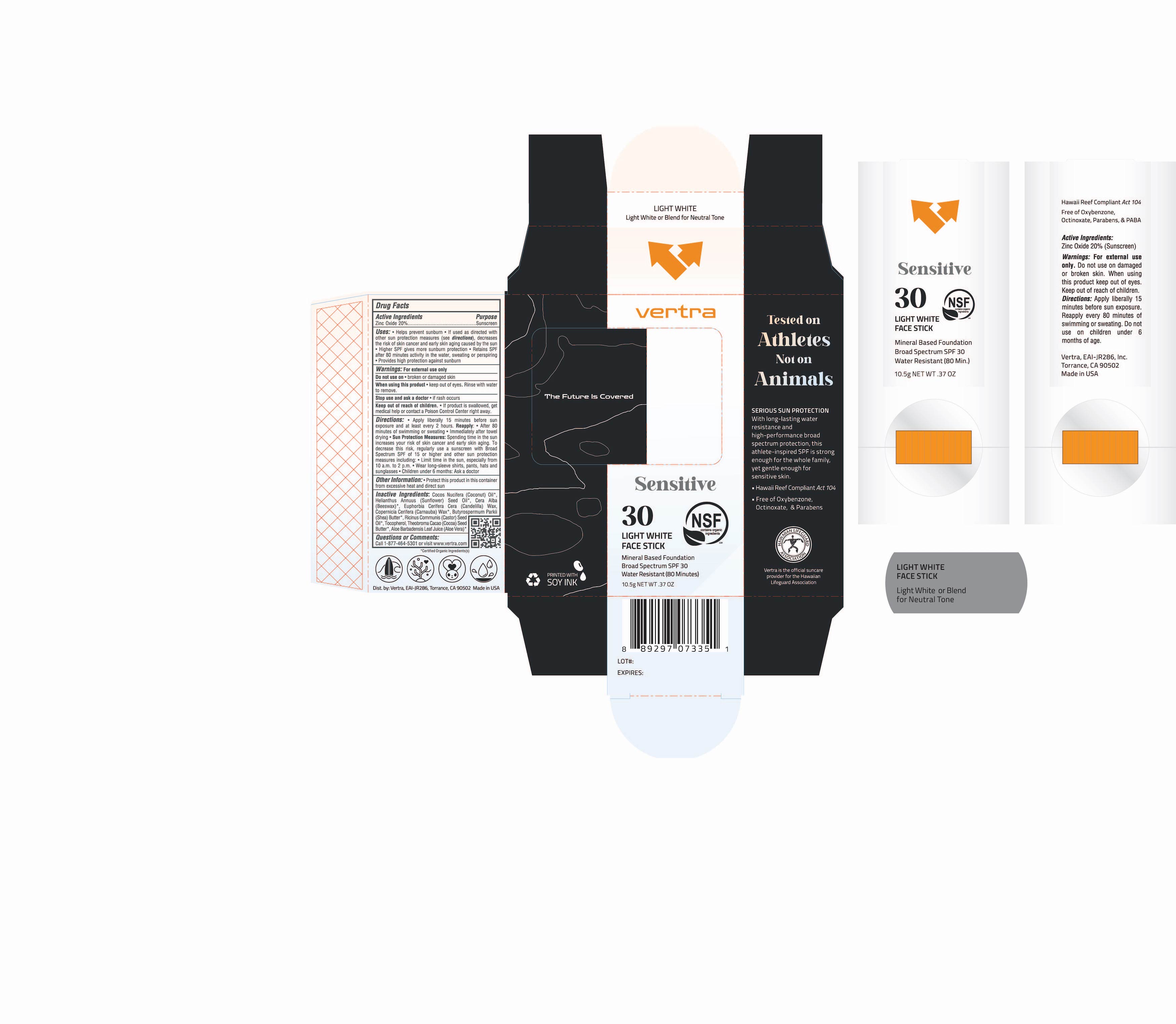 DRUG LABEL: Clear Sunscreen Face Stick Sensitive Broad Spectrum SPF 30
NDC: 71014-091 | Form: STICK
Manufacturer: EAI-JR 286, Inc
Category: otc | Type: HUMAN OTC DRUG LABEL
Date: 20241022

ACTIVE INGREDIENTS: ZINC OXIDE 20 g/100 g
INACTIVE INGREDIENTS: WHITE WAX; SHEA BUTTER; TOCOPHEROL; CASTOR OIL; COCOA BUTTER; COCONUT OIL; SUNFLOWER OIL; ALOE VERA LEAF; CANDELILLA WAX; CARNAUBA WAX

Clear Sunscreen Face Stick Sensitive Broad Spectrum SPF 30

Active Ingredients Purpose

Zinc Oxide 20% Sunscreen

Uses

- Helps prevent Sunburn
- If used as directed with other sun protection measures (see Directions), decreases the risk of skin cancer and early skin aging caused by the sun
- Higher SPF gives more sunburn protection
- Retains SPF after 80 minutes activity in the water, sweating or perspiring
- Provides high protection against sunburn

Keep out of reach of children:

- If product is swallowed, get medical help or contact a Poison Control Center right away.

Stop use and ask a doctor if:

- Rash or irritation develops and lasts

Warnings

Do not use:

- On damaged or broken skin

When using this product:

- keep out of eyes. Rinse with water to remove
- For external use only

Directions

- Apply liberally and generously 15 minutes before sun exposure and at least every 2 hours.
- Children under 6 months of age: ask a doctor.
- Sun Proctection Measures Spending time in the sun increases your risk of skin cancer and early sking aging. To decrease this risk, regularly use a sunscreen with a Broad Spectrum SPF value of 15 or higher and other sun protection measures including:
- Limit your time in the sun, especially from 10 a.m. - 2 p.m.
- Wear long-sleeved shirts, pants, hats, and sunglasses
- Reapply:
- After 80 minutes of swimming or sweating
- Immediately after towel drying
- At least every 2 hours

Inactive ingredient

Cocos Nucifera (Coconut) Oil, Helianthus Annuus (Sunflower) Seed Oil, Cera Alba (Beeswax), Euphorbia Cerifera Cera (Candelilla) Wax, Copernicia Cerifera (Carnauba) Wax, Butyrospermum Parkii (Shea) Butter, Ricinus Communis (Castor) Seed Oil, Tocopherol, Theobroma Cacao (Cocoa) Seed Butter, Aloe Barbadensis Leaf Juice (Aloe Vera),

Other Information

Protect this product in this container from excessive heat and direct sun

PACKAGE LABEL

vertra

Sensitive

30

Light White Face Stick

Mineral Based Foundation

Broad Spectrum SPF 30

Water Resistant (80 minutes)

10.5 g NET WT. 0.37 OZ.